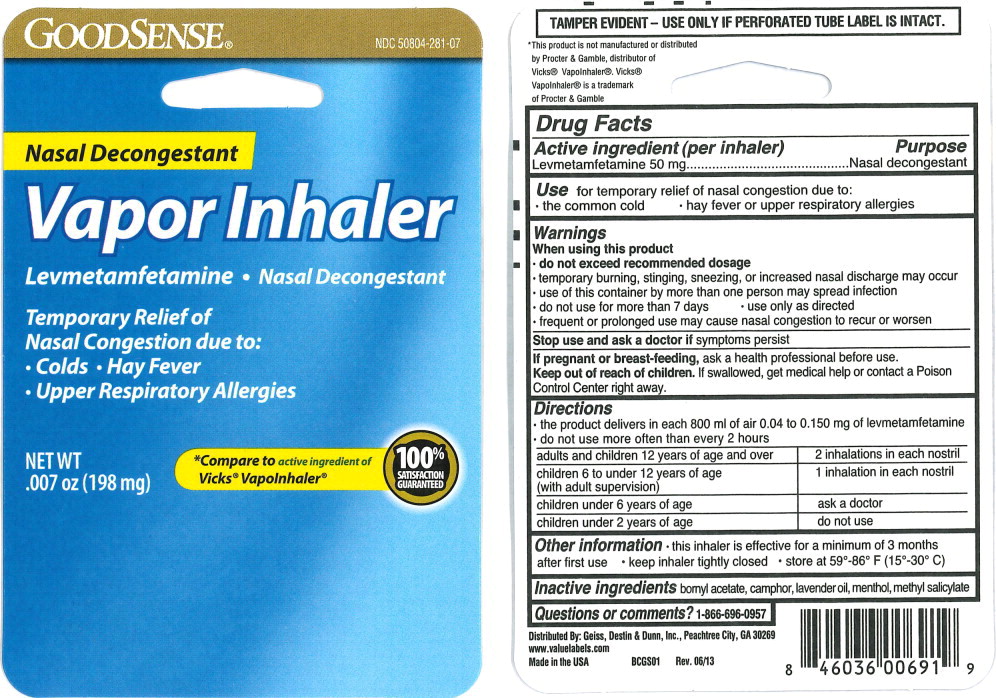 DRUG LABEL: Vapor Inhaler 
NDC: 50804-281 | Form: INHALANT
Manufacturer: Geiss, Destin & Dunn, Inc.
Category: otc | Type: HUMAN OTC DRUG LABEL
Date: 20250919

ACTIVE INGREDIENTS: Levmetamfetamine 50 mg/1 1
INACTIVE INGREDIENTS: Bornyl acetate; Camphor (Synthetic); Lavender oil; Menthol; Methyl Salicylate

Drug Facts

Active ingredient (per inhaler)

Levmetamfetamine 50 mg

Purpose

Nasal decongestant

Use

for temporary relief of nasal congestion due to:

- the common cold
- hay fever or upper respiratory allergies

Warnings

When using this product

- do not exceed recommended dosage
- temporary burning, stinging, sneezing, or increased nasal discharge may occur
- use of this container by more than one person may spread infection

- do not use for more than 7 days
- use only as directed
- frequent or prolonged use may cause nasal congestion to recur or worsen

Stop use and ask a doctor if symptoms persist

PREGNANCY OR BREAST FEEDING

If pregnant or breast-feeding, ask a health professional before use.

Keep out of reach of children. If swallowed, get medical help or contact a Poison Control Center right away.

Directions

- the product delivers in each 800 ml of air 0.04 to 0.150 mg of levmetamfetamine
- do not use more often than every 2 hours

adults and children 12 years of age and over | 2 inhalations in each nostril
children 6 to under 12 years of age (with adult supervision) | 1 inhalation in each nostril
children under 6 years of age | ask a doctor
children under 2 years of age | do not use

Other information

- this inhaler is effective for a minimum of 3 months after first use
- keep inhaler tightly closed
- store at 59°-86° F (15°-30° C)

Inactive ingredients

bornyl acetate, camphor, lavender oil, menthol, methyl salicylate

Questions or comments?

1-866-696-0957

Principal Display Panel - 198 mg Blister Pack Label

GOODSENSE®

NDC 50804-281-07

Nasal Decongestant

Vapor Inhaler

Levmetamfetamine • Nasal Decongestant

Temporary Relief of
Nasal Congestion due to:

- Colds • Hay Fever
- Upper Respiratory Allergies

NET WT
.007 oz (198 mg)

*Compare to active ingredient of
Vicks® Vapolnhaler®

100%
SATISFACTION
GUARANTEED